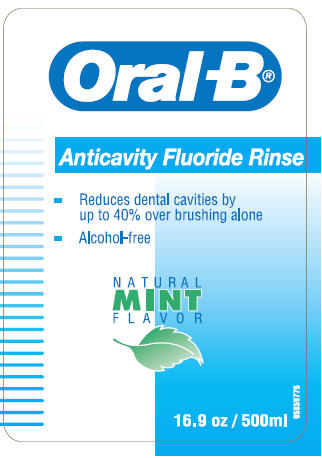 DRUG LABEL: Oral-B 
NDC: 0041-1421 | Form: LIQUID
Manufacturer: Oral-B Laboratories
Category: otc | Type: HUMAN OTC DRUG LABEL
Date: 20100402

ACTIVE INGREDIENTS: Sodium Fluoride 500 ug/1 mL

Oral-B®
Anticavity Fluoride Rinse

Drug Facts

Active ingredient

Sodium Fluoride 0.05%

Purpose

Anticavity

Use

Aids in the prevention of dental cavities.

Warnings

Keep out of the reach of children.

Do not use if shrinkband is broken or missing.

WHEN USING

Do not swallow.

If more than amount used for rinsing is accidentally swallowed, seek professional assistance or contact a Poison Control Center immediately.

Directions

- Adults and children 6 years and older: use once a day after brushing your teeth with toothpaste.
- Vigorously swish 10ml (as indicated inside cap) of rinse between your teeth for 1 minute then spit out. Do not swallow.
- Do not eat or drink for 30 minutes after rinsing.
- Instruct children under 12 years of age in good rinsing habits to minimize swallowing.
- Supervise children as necessary until capable of using without supervision.
- Consult a dentist or physician for use by children under 6 years of age.

Other information

Store above freezing.

Inactive ingredients

Water, Glycerin, PEG 40 Hydrogenated Castor Oil, Flavor, Sodium Benzoate, Potassium Sorbate, Phosphoric Acid, Sodium Saccharin, FD&C Blue #1

Question or comments?

1-800-56-ORALB www.oralb.com

Distributed by:
Oral-B, A Division of
Procter & Gamble
Cincinnati, OH 45202
© Oral-B Laboratories

Made in Colombia

PRINCIPAL DISPLAY PANEL - 500ml Label

Oral -B®

Anticavity Fluoride Rinse

- Reduces dental cavities by
  up to 40% over brushing alone
- Alcohol-free

NATURAL
MINT
FLAVOR

16.9 oz / 500ml